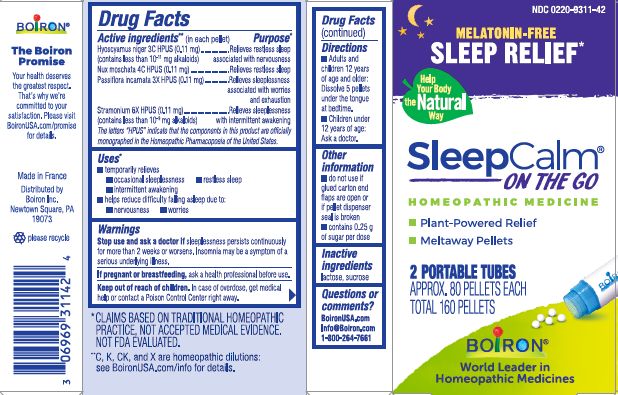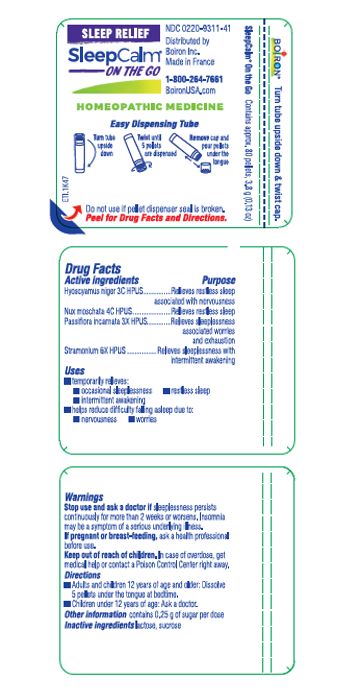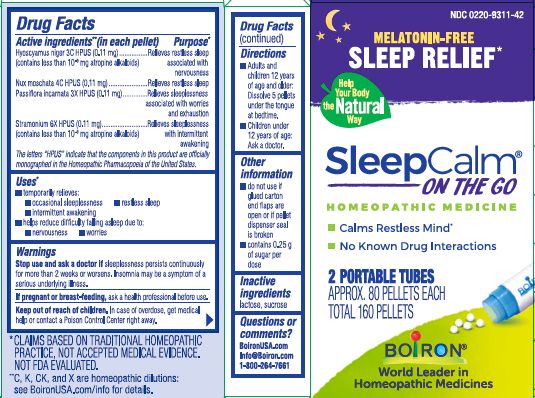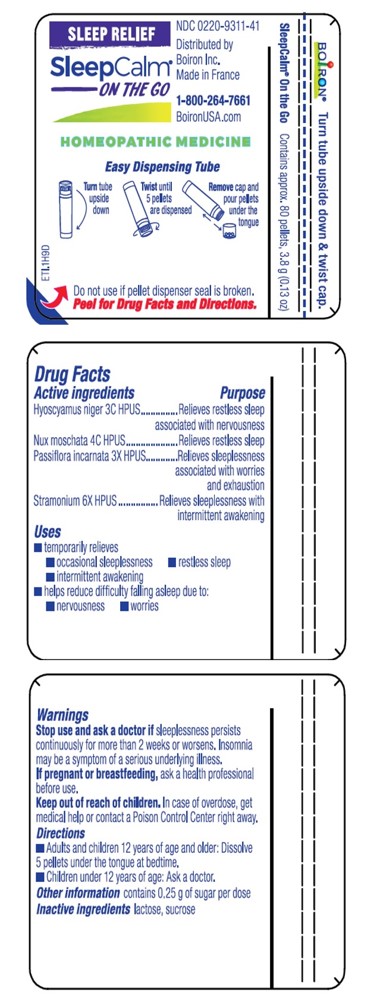 DRUG LABEL: SleepCalm
NDC: 0220-9311 | Form: PELLET
Manufacturer: Boiron
Category: homeopathic | Type: HUMAN OTC DRUG LABEL
Date: 20240423

ACTIVE INGREDIENTS: HYOSCYAMUS NIGER 3 [hp_C]/1 1; DATURA STRAMONIUM 6 [hp_X]/1 1; PASSIFLORA INCARNATA TOP 3 [hp_X]/1 1; NUTMEG 4 [hp_C]/1 1
INACTIVE INGREDIENTS: LACTOSE, UNSPECIFIED FORM; SUCROSE

SleepCalm Pellets

Active ingredients** (in each pellet)

Hyoscyamus niger 3C HPUS (0.11 mg) (contains less than 10^-9 mg atropine alkaloids)

Nux moschata 4C HPUS (0.11 mg)

Passiflora incarnata 3X HPUS (0.11 mg)

Stramonium 6X HPUS (0.11 mg) (contains less than 10^-9 mg atropine alkaloids)

The letters "HPUS" indicate that the components in this product are officially monographed in the Homeopathic Pharmacopoeia of the United States.

PURPOSE

Hyoscyamus niger 3C HPUS (0.11 mg) ... Relieves restless sleep associated with nervousness

Nux moschata 4C HPUS (0.11 mg) ... Relieves restless sleep

Passiflora incarnata 3X HPUS (0.11 mg) ... Relieves sleeplessness associated with worries and exhaustion

Stramonium 6X HPUS (0.11 mg) ... Relieves sleeplessness with intermittent awakening

Uses*

- temporarily relieves:
- occasional sleeplessness
- restless sleep
- intermittent awakening

- helps reduce difficulty falling asleep due to:
- nervousness
- worries

Stop use and ask a doctor if sleeplessness persists continuously for more than 2 weeks or worsens. Insomnia may be a symptom of a serious underlying illness.

PREGNANCY OR BREAST FEEDING

If pregnant or breast-feeding, ask a health professional before use.

Keep out of reach of children. In case of overdose, get medical help or contact a Poison Control Center right away.

Directions

- Adults and children 12 years of age and older: Dissolve 5 pellets under the tongue at bedtime.
- Children under 12 years of age: Ask a doctor.

INACTIVE INGREDIENT

lactose, sucrose

QUESTIONS

BoironUSA.com

Info@Boiron.Com

1-800-264-7661

Made in France

Distributed by

Boiron, Inc.

Newtown Square, PA 19073

Melatonin-Free

Sleep Relief*

do not use if glued carton end flaps are open or if pellet dispenser seal is broken

contains 0.25 g of sugar per dose

Calms Restless Mind*

No Known Drug Interactions

2 PORTABLE TUBES

APPROX. 80 PELLETS EACH

TOTAL 160 PELLETS

Tube - Contains approx. 80 pellets, 3.8g, (0.13 oz)

Tube - Do not use if pellet dispenser seal is broken.

Turn tube upside down

Twist until 5 pellets are dispensed

Remove cap and pour pellets under the tongue

*CLAIMS BASED ON TRADITIONAL HOMEOPATHIC PRACTICE NOT ACCEPTED MEDICAL EVIDENCE. NOT FDA EVALUATED.
**C,K,CK, and X are homeopathic dilutions: see BoironUSA.com/info for details.